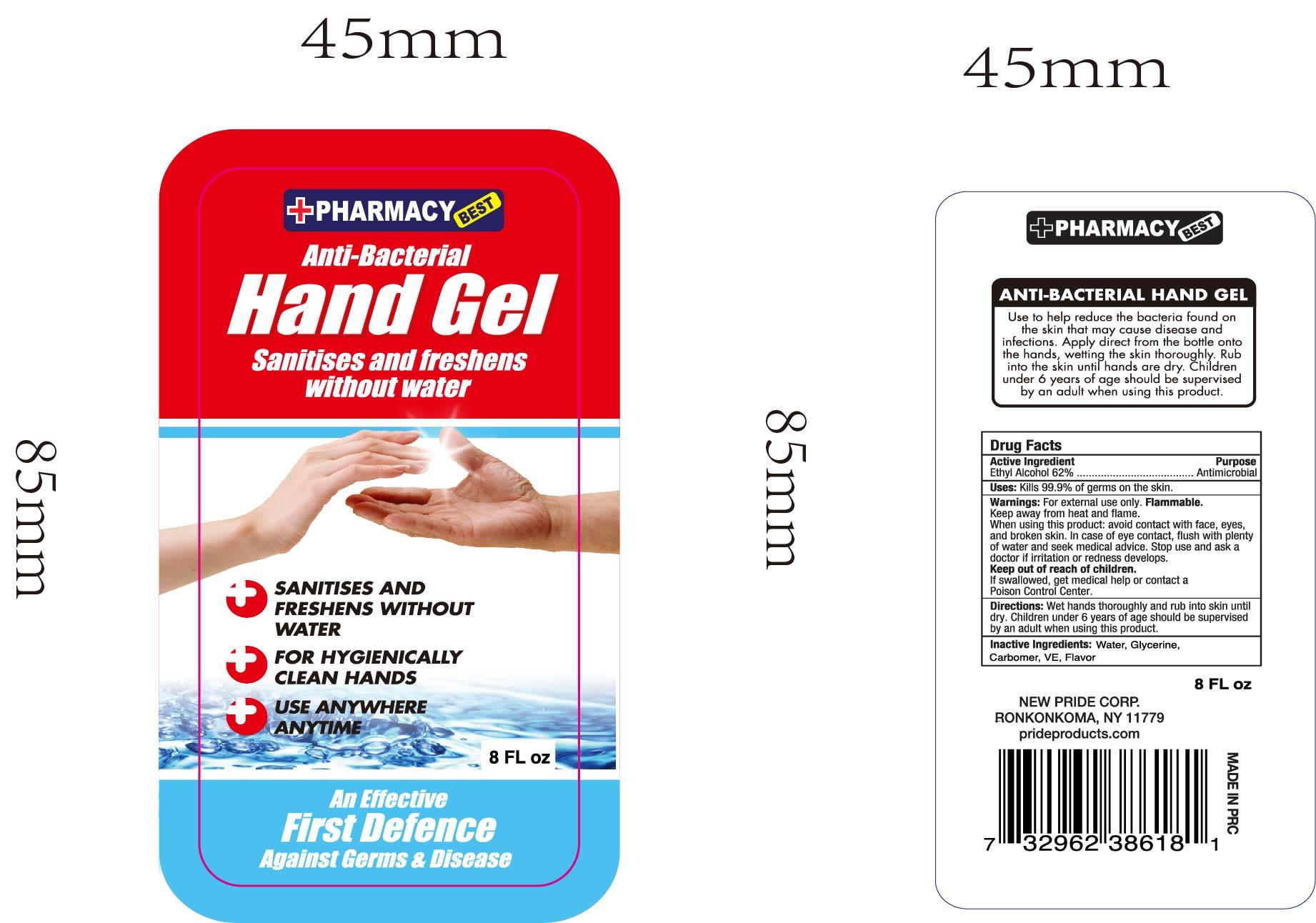 DRUG LABEL: Hand Sanitizer
NDC: 73946-002 | Form: GEL
Manufacturer: Yiwu Jiefei Daily Chemicals Co.,Ltd.
Category: otc | Type: HUMAN OTC DRUG LABEL
Date: 20200403

ACTIVE INGREDIENTS: ALCOHOL 62 mL/100 mL
INACTIVE INGREDIENTS: GLYCERIN; CARBOMER 934; WATER

73946-002 Hand Sanitizer

Active Ingredient(s)

Isopropyl Alcohol 62% v/v. Purpose: Antimicarobial

Purpose

Antimicrobial

Use

Kills 99.9% of germs on the skin.

Warnings

Warnings: For extermnal use only. Flammable.
Keep away from heat and flame.
When using this product: avoid contact with face, eyes,
and broken skin. In case of eye contact, flush with plenty
of water and seek medical advice. Stop use and ask a
doctor if rritation or redness develops.
Keep out of reach of children. .
If swallowed, get medical help or contact a
Poison Control Center.

Keep out of reach of children. If swallowed, get medical help or contact a Poison Control Center

Directions

Directions: Wet hands thoroughly and rub into skin until
dry. Children under 6 years of age should be supervised
by an adult when using this product.

Inactive ingredients

Inactive Ingredients: Water, Glycerine,
Carbomer, VE, Flavor